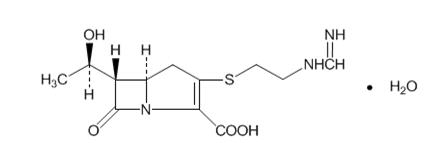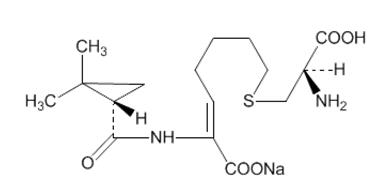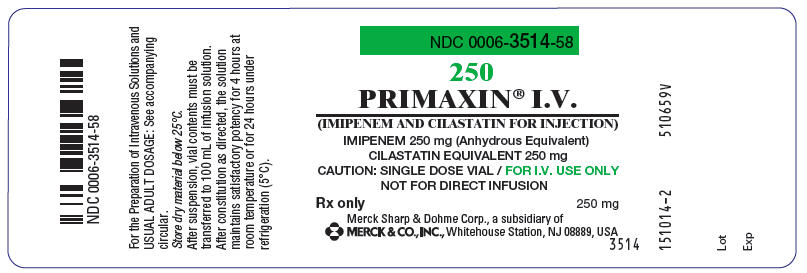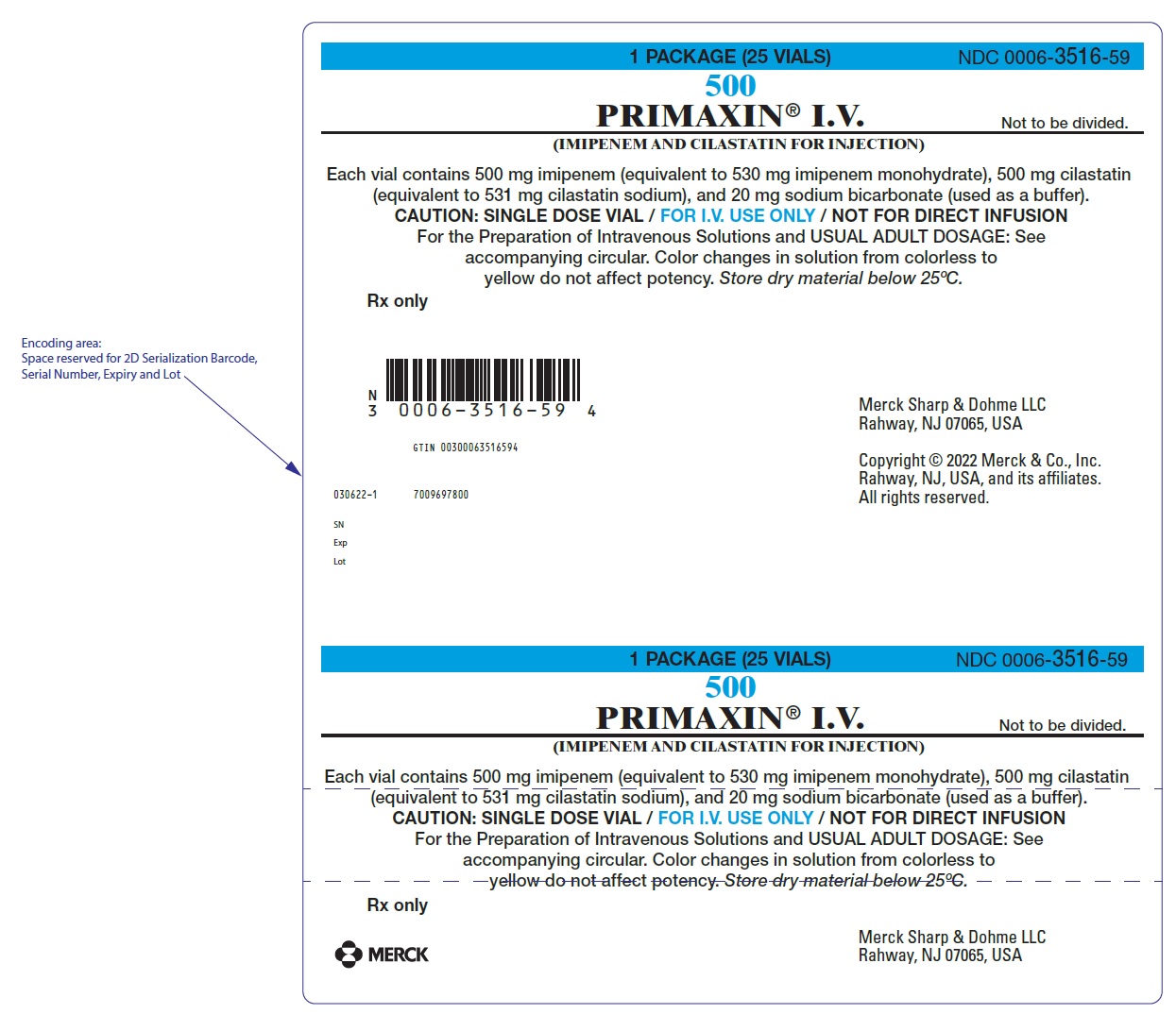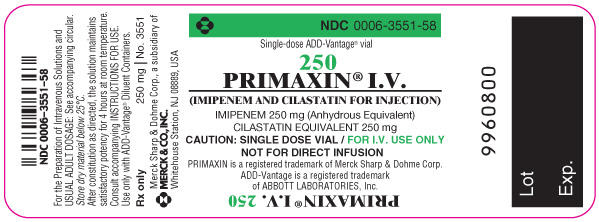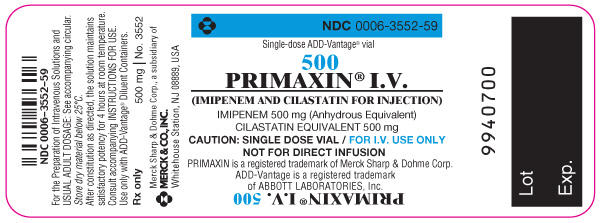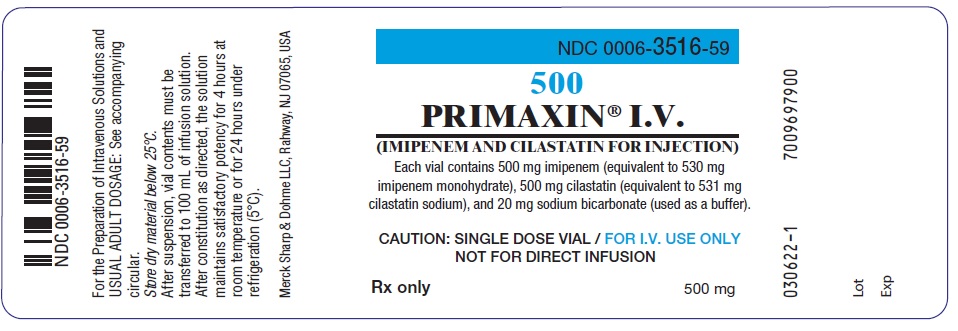 DRUG LABEL: PRIMAXIN
NDC: 0006-3514 | Form: INJECTION, POWDER, FOR SOLUTION
Manufacturer: Merck Sharp & Dohme LLC
Category: prescription | Type: HUMAN PRESCRIPTION DRUG LABEL
Date: 20240705

ACTIVE INGREDIENTS: IMIPENEM 250 mg/100 mL; CILASTATIN SODIUM 250 mg/100 mL
INACTIVE INGREDIENTS: SODIUM BICARBONATE 10 mg/100 mL

HIGHLIGHTS OF PRESCRIBING INFORMATION

These highlights do not include all the information needed to use PRIMAXIN safely and effectively. See full prescribing information for PRIMAXIN.
PRIMAXIN® (imipenem and cilastatin) for Injection, for intravenous use
Initial U.S. Approval: 1985

1 INDICATIONS AND USAGE

PRIMAXIN for intravenous use is a combination of imipenem, a penem antibacterial, and cilastatin, a renal dehydropeptidase inhibitor, indicated for the treatment of the following serious infections caused by designated susceptible bacteria:

- Lower respiratory tract infections. (1.1)
- Urinary tract infections. (1.2)
- Intra-abdominal infections. (1.3)
- Gynecologic infections. (1.4)
- Bacterial septicemia. (1.5)
- Bone and joint infections. (1.6)
- Skin and skin structure infections. (1.7)
- Endocarditis. (1.8)

Limitations of Use:

- PRIMAXIN is not indicated in patients with meningitis because safety and efficacy have not been established (1.9).
- PRIMAXIN is not recommended in pediatric patients with CNS infections because of the risk of seizures (1.9).
- PRIMAXIN is not recommended in pediatric patients weighing less than 30 kg with impaired renal function (1.9).

Usage:

To reduce the development of drug resistant bacteria and maintain the effectiveness of PRIMAXIN and other antibacterial drugs, PRIMAXIN should be used only to treat infections that are proven or strongly suspected to be caused by bacteria (1.10).

2 DOSAGE AND ADMINISTRATION

- The dosage of PRIMAXIN in adult patients should be based on suspected or confirmed pathogen susceptibility (2.1).
- For adult patients with normal renal function (creatinine clearance of greater than or equal to 90 mL/min), the recommended dosage regimens are: 500 mg every 6 hours OR 1000 mg every 8 hours OR 1000 mg every 6 hours (2.1).
- See full prescribing information for dosage recommendations in pediatric patients (2.2).
- A reduction in dose must be made for a patient with a creatinine clearance of less than 90 mL/min (2.3).
- Patients with creatinine clearances of less than 15 mL/min should not receive PRIMAXIN unless hemodialysis is instituted within 48 hours (2.4).
- Reconstitute PRIMAXIN vial with appropriate diluent and dilute the reconstituted suspension with an appropriate infusion solution before administering by intravenous infusion (2.5).

3 DOSAGE FORMS AND STRENGTHS

For Injection: PRIMAXIN is a sterile powder mixture for reconstitution in single-dose containers including vials containing:

- 500 mg imipenem (anhydrous equivalent) and 500 mg cilastatin (free acid equivalent) (3)

4 CONTRAINDICATIONS

- Known hypersensitivity to any component of PRIMAXIN (4)

5 WARNINGS AND PRECAUTIONS

- Hypersensitivity Reactions: Serious and occasionally fatal hypersensitivity (anaphylactic) reactions have been reported in patients receiving therapy with beta-lactams. If an allergic reaction to PRIMAXIN occurs, discontinue the drug immediately (5.1).
- Seizure Potential: Seizures and other CNS adverse reactions, such as confusional states and myoclonic activity, have been reported during treatment with PRIMAXIN. If focal tremors, myoclonus, or seizures occur, patients should be evaluated neurologically, placed on anticonvulsant therapy if not already instituted, and the dosage of PRIMAXIN re-examined to determine whether it should be decreased, or the antibacterial drug discontinued (5.2).
- Increased Seizure Potential Due to Interaction with Valproic Acid: Co-administration of PRIMAXIN, to patients receiving valproic acid or divalproex sodium results in a reduction in valproic acid concentrations. The valproic acid concentrations may drop below the therapeutic range as a result of this interaction, therefore increasing the risk of breakthrough seizures. The concomitant use of PRIMAXIN and valproic acid/divalproex sodium is generally not recommended (5.3, 7.3).
- Clostridioides difficile-Associated Diarrhea (CDAD): has been reported with use of PRIMAXIN and may range in severity from mild diarrhea to fatal colitis. Evaluate if diarrhea occurs (5.4).

6 ADVERSE REACTIONS

- The most frequently occurring adverse reactions (≥0.2%) in adults were phlebitis, nausea, diarrhea, vomiting, rash, pain injection site, fever, hypotension, seizures, erythema at injection site, dizziness, pruritus, vein induration, urticaria, somnolence (6.1).
- The most frequently occurring adverse reactions (>1%) in pediatric patients greater than or equal to 3 months of age were diarrhea, rash, phlebitis, gastroenteritis, vomiting, IV site irritation, urine discoloration (6.1).
- The most frequently occurring adverse reactions (>1%) in neonates to 3 months of age were convulsions, diarrhea, oliguria/anuria, oral candidiasis, rash, tachycardia (6.1).

To report SUSPECTED ADVERSE REACTIONS, contact Merck Sharp & Dohme LLC at 1-877-888-4231 or FDA at 1-800-FDA-1088 or www.fda.gov/medwatch .

7 DRUG INTERACTIONS

- Ganciclovir: Generalized seizures have been reported in patients who received ganciclovir. Do not co-administer unless benefit outweighs risk (7.1).
- Probenecid: Concomitant administration of PRIMAXIN and probenecid results in increases in the plasma level and half-life of imipenem. Concomitant administration is not recommended (7.2).
- Valproic acid/divalproex sodium: Concomitant use with PRIMAXIN is generally not recommended. Consider other antibacterial drugs to treat infections in patients whose seizures are well-controlled on valproic acid or divalproex sodium (5.3, 7.3).

8 USE IN SPECIFIC POPULATIONS

- Renal Impairment: Dosage adjustment is necessary in patients with renal impairment (2.3).
  - Adult patients with creatinine clearances of less than or equal to 30 mL/min, whether or not undergoing hemodialysis, had a higher risk of seizure activity than those without impairment of renal function (5.2).
  - Therefore, close adherence to the dosing guidelines and regular monitoring of creatinine clearance for these patients is recommended (8.6).

FULL PRESCRIBING INFORMATION

1 INDICATIONS AND USAGE

1.1 Lower Respiratory Tract Infections

PRIMAXIN for intravenous use is indicated for the treatment of lower respiratory tract infections caused by susceptible strains of Staphylococcus aureus (penicillinase-producing isolates), Acinetobacter species, Enterobacter species, Escherichia coli, Haemophilus influenzae, Haemophilus parainfluenzae, Klebsiella species, Serratia marcescens.

1.2 Urinary Tract Infections (complicated and uncomplicated)

PRIMAXIN is indicated for the treatment of urinary tract infections (complicated and uncomplicated) caused by susceptible strains of Enterococcus faecalis, Staphylococcus aureus (penicillinase-producing isolates), Enterobacter species, Escherichia coli, Klebsiella species, Morganella morganii, Proteus vulgaris, Providencia rettgeri, Pseudomonas aeruginosa.

1.3 Intra-Abdominal Infections

PRIMAXIN is indicated for the treatment of intra-abdominal infections caused by susceptible strains of Enterococcus faecalis, Staphylococcus aureus (penicillinase-producing isolates), Staphylococcus epidermidis, Citrobacter species, Enterobacter species, Escherichia coli, Klebsiella species, Morganella morganii, Proteus species, Pseudomonas aeruginosa, Bifidobacterium species, Clostridium species, Eubacterium species, Peptococcus species, Peptostreptococcus species, Propionibacterium species, Bacteroides species including B. fragilis, Fusobacterium species.

1.4 Gynecologic Infections

PRIMAXIN is indicated for the treatment of gynecologic infections caused by susceptible strains of Enterococcus faecalis, Staphylococcus aureus (penicillinase-producing isolates), Staphylococcus epidermidis, Streptococcus agalactiae (Group B streptococci), Enterobacter species, Escherichia coli, Gardnerella vaginalis, Klebsiella species, Proteus species, Bifidobacterium species, Peptococcus species, Peptostreptococcus species, Propionibacterium species, Bacteroides species including B. fragilis.

1.5 Bacterial Septicemia

PRIMAXIN is indicated for the treatment of bacterial septicemia caused by susceptible strains of Enterococcus faecalis, Staphylococcus aureus (penicillinase-producing isolates), Enterobacter species, Escherichia coli, Klebsiella species, Pseudomonas aeruginosa, Serratia species, Bacteroides species including B. fragilis.

1.6 Bone and Joint Infections

PRIMAXIN is indicated for the treatment of bone and joint infections caused by susceptible strains of Enterococcus faecalis, Staphylococcus aureus (penicillinase-producing isolates), Staphylococcus epidermidis, Enterobacter species, Pseudomonas aeruginosa.

1.7 Skin and Skin Structure Infections

PRIMAXIN is indicated for the treatment of skin and skin structure infections caused by susceptible strains of Enterococcus faecalis, Staphylococcus aureus (penicillinase-producing isolates), Staphylococcus epidermidis, Acinetobacter species, Citrobacter species, Enterobacter species, Escherichia coli, Klebsiella species, Morganella morganii, Proteus vulgaris, Providencia rettgeri, Pseudomonas aeruginosa, Serratia species, Peptococcus species, Peptostreptococcus species, Bacteroides species including B. fragilis, Fusobacterium species.

1.8 Endocarditis

PRIMAXIN is indicated for the treatment of endocarditis caused by susceptible strains of Staphylococcus aureus (penicillinase-producing isolates).

1.9 Limitations of Use

- PRIMAXIN is not indicated in patients with meningitis because safety and efficacy have not been established.
- PRIMAXIN is not recommended in pediatric patients with CNS infections because of the risk of seizures [see Dosage and Administration (2.2), Warnings and Precautions (5.2), and Use in Specific Populations (8.4)].
- PRIMAXIN is not recommended in pediatric patients less than 30 kg with impaired renal function, as no data are available [see Use in Specific Populations (8.4), and Dosage and Administration (2.2)].
- Periodic assessment of organ system functions, including renal, hepatic and hematopoietic, is advisable during prolonged therapy.

1.10 Usage

To reduce the development of drug-resistant bacteria and maintain the effectiveness of PRIMAXIN and other antibacterial drugs, PRIMAXIN should be used only to treat infections that are proven or strongly suspected to be caused by susceptible bacteria. When culture and susceptibility information are available, they should be considered in selecting or modifying antibacterial therapy. In the absence of such data, local epidemiology and susceptibility patterns may contribute to the empiric selection of therapy.

2 DOSAGE AND ADMINISTRATION

2.1 Dosage in Adults

For Intravenous Injection Only

- The dosage of PRIMAXIN in adult patients should be based on suspected or confirmed pathogen susceptibility as shown in Table 1 below. The dosage recommendations for PRIMAXIN represent the quantity of imipenem to be administered. An equivalent amount of cilastatin is also present in the solution.
- These doses should be used for patients with creatinine clearance of greater than or equal to 90 mL/min. A reduction in dose must be made for patients with creatinine clearance less than 90 mL/min as shown in Table 3 [see Dosage and Administration (2.3)].
- Recommend that the maximum total daily dosage not exceed 4 g/day.
- Administer 500 mg by intravenous infusion over 20 to 30 minutes.
- Administer 1000 mg by intravenous infusion over 40 to 60 minutes.
- In patients who develop nausea during the infusion, the rate of infusion may be slowed.

Table 1: Dosage of PRIMAXIN in Adult Patients with Creatinine Clearance Greater than or Equal to 90 mL/min
Suspected or Proven Pathogen Susceptibility | Dosage of PRIMAXIN
If the infection is suspected or proven to be due to a susceptible bacterial species | 500 mg every 6 hours OR 1000 mg every 8 hours
If the infection is suspected or proven to be due to bacterial species with intermediate susceptibility [see Microbiology (12.4)] | 1000 mg every 6 hours

2.2 Dosage in Pediatric Patients

PRIMAXIN is not recommended in pediatric patients with CNS infections because of the risk of seizures [see Use in Specific Populations (8.4)].

PRIMAXIN is not recommended in pediatric patients <30 kg with renal impairment, as no data are available [see Use in Specific Populations (8.4)].

Based on studies in adults, the maximum total daily dose in pediatric patients should not exceed 4 g/day [see Dosage and Administration (2.1)].

The recommended dosage for pediatric patients with non-CNS infections is shown in Table 2 below:

Table 2: Recommended PRIMAXIN Dosage in Pediatric Patients for Non-CNS Infections
Age | Dose (mg/kg) [Doses less than or equal to 500 mg should be given by intravenous infusion over 20 to 30 minutes] , [Doses greater than 500 mg should be given by intravenous infusion over 40 to 60 minutes Recommend that the maximum total daily dosage not exceed 4g/day] | Frequency (hours)
Greater than or equal to 3 Months of Age
 | 15-25 mg/kg | Every 6 hours
Less than or equal to 3 months of age (Greater than or equal to 1,500 g body weight)
4 weeks to 3 months of age | 25 mg/kg | Every 6 hours
1 to 4 weeks of age | 25 mg/kg | Every 8 hours
Less than 1 week of age | 25 mg/kg | Every 12 hours

2.3 Dosage in Adult Patients with Renal Impairment

Patients with creatinine clearance less than 90 mL/min require dosage reduction of PRIMAXIN as indicated in Table 3. The serum creatinine should represent a steady state of renal function. Use the Cockcroft-Gault method described below to calculate the creatinine clearance:

Males: | (weight in kg) × (140-age in years)
 | (72) × serum creatinine (mg/100 mL)
Females: | (0.85) × (value calculated for males)

Table 3: Dosage of PRIMAXIN for Adult Patients in Various Renal Function Groups Based on Estimated Creatinine Clearance (CLcr)
 | Creatinine clearance (mL/min)
 | Greater than or equal to 90 | Less than 90 to greater than or equal to 60 | Less than 60 to greater than or equal to 30 | Less than 30 to greater than or equal to 15
Dosage of PRIMAXIN [Administer doses less than or equal to 500 mg by intravenous infusion over 20 to 30 minutes. Discard unused portion of the infusion solution.] , [Administer doses greater than 500 mg by intravenous infusion over 40 to 60 minutes. In patients who develop nausea during the infusion, the rate of infusion may be slowed.] If the infection is suspected or proven to be due to a susceptible bacterial species: | 500 mg every 6 hours | 400 mg every 6 hours | 300 mg every 6 hours | 200 mg every 6 hours
Dosage of PRIMAXIN [Administer doses less than or equal to 500 mg by intravenous infusion over 20 to 30 minutes. Discard unused portion of the infusion solution.] , [Administer doses greater than 500 mg by intravenous infusion over 40 to 60 minutes. In patients who develop nausea during the infusion, the rate of infusion may be slowed.] If the infection is suspected or proven to be due to a susceptible bacterial species: | OR
Dosage of PRIMAXIN [Administer doses less than or equal to 500 mg by intravenous infusion over 20 to 30 minutes. Discard unused portion of the infusion solution.] , [Administer doses greater than 500 mg by intravenous infusion over 40 to 60 minutes. In patients who develop nausea during the infusion, the rate of infusion may be slowed.] If the infection is suspected or proven to be due to a susceptible bacterial species: | 1000 mg every 8 hours | 500 mg every 6 hours | 500 mg every 8 hours | 500 mg every 12 hours
Dosage of PRIMAXIN, If the infection is suspected or proven to be due to bacterial species with intermediate susceptibility [see Microbiology (12.4)]: | 1000 mg every 6 hours | 750 mg every 8 hours | 500 mg every 6 hours | 500 mg every 12 hours

In patients with creatinine clearances of less than 30 to greater than or equal to 15 mL/min, there may be an increased risk of seizures [see Warnings and Precautions (5.2) and Use in Specific Populations (8.6)]. Patients with creatinine clearance less than 15 mL/min should not receive PRIMAXIN unless hemodialysis is instituted within 48 hours. There is inadequate information to recommend usage of PRIMAXIN for patients undergoing peritoneal dialysis.

2.4 Dosage in Hemodialysis Patients

When treating patients with creatinine clearances of less than 15 mL/min who are undergoing hemodialysis, use the dosage recommendations for patients with creatinine clearances of less than 30 to greater than or equal to 15 mL/min in Table 3 above [see Dosage and Administration (2.3)]. Both imipenem and cilastatin are cleared from the circulation during hemodialysis. The patient should receive PRIMAXIN after hemodialysis and at intervals timed from the end of that hemodialysis session. Dialysis patients, especially those with background CNS disease, should be carefully monitored; for patients on hemodialysis, PRIMAXIN is recommended only when the benefit outweighs the potential risk of seizures [see Warnings and Precautions (5.2)].

2.5 Reconstitution and Preparation of PRIMAXIN Solution for Intravenous Administration

PRIMAXIN Vials

- Do not use diluents containing benzyl alcohol to reconstitute PRIMAXIN for administration to neonates because it has been associated with toxicity in neonates. While toxicity has not been demonstrated in pediatric patients greater than three months of age, small pediatric patients in this age range may also be at risk for benzyl alcohol toxicity.
- Contents of the vials must be reconstituted by adding approximately 10 mL of the appropriate diluent to the vial. List of appropriate diluents are as follows:
  - 0.9% Sodium Chloride Injection
  - 5% Dextrose Injection
  - 5% Dextrose and 0.9% Sodium Chloride Injection
  - 5% Dextrose Injection with 0.225% or 0.45% saline solution
- Reconstituted Solutions of PRIMAXIN range from colorless to yellow. Variations of color within this range do not affect the potency of the product.
- The reconstituted suspension must not be administered by direct Intravenous Infusion
- After reconstitution, shake vial well and transfer the resulting suspension to 100 mL of an appropriate infusion solution before administering by intravenous infusion.
- Repeat transfer of the resulting suspension with an additional 10 mL of infusion solution to ensure complete transfer of vial contents to the infusion solution. Agitate the resulting mixture until clear.
- Parenteral drug products should be inspected visually for particulate matter and discoloration prior to administration, whenever solution and container permit.
- Discard unused portion of the infusion solution where applicable.

2.6 Storage of Reconstituted Solutions

Vials (After Reconstitution)

- PRIMAXIN, as supplied in single dose vials and reconstituted with the appropriate diluents [see Dosage and Administration (2.5)], maintains satisfactory potency for 4 hours at room temperature or for 24 hours under refrigeration (5°C). Do not freeze solutions of PRIMAXIN.

2.7 Incompatibility and Compatibility of PRIMAXIN with other Antibacterial Drugs

- Do not mix PRIMAXIN with, or physically add to, other antibacterial drugs.
- PRIMAXIN may be administered concomitantly with other antibacterial drugs, such as aminoglycosides.

3 DOSAGE FORMS AND STRENGTHS

For Injection PRIMAXIN is a sterile powder mixture for reconstitution in single-dose containers including vials containing:

- 500 mg imipenem (anhydrous equivalent) and 500 mg cilastatin (free acid equivalent)

4 CONTRAINDICATIONS

PRIMAXIN is contraindicated in patients who have shown hypersensitivity to any component of this product.

5 WARNINGS AND PRECAUTIONS

5.1 Hypersensitivity Reactions

Serious and occasionally fatal hypersensitivity (anaphylactic) reactions have been reported in patients receiving therapy with beta-lactams. These reactions are more likely to occur in individuals with a history of sensitivity to multiple allergens. There have been reports of individuals with a history of penicillin hypersensitivity who have experienced severe hypersensitivity reactions when treated with another beta-lactam. Before initiating therapy with PRIMAXIN, careful inquiry should be made concerning previous hypersensitivity reactions to penicillins, cephalosporins, other beta-lactams and other allergens. If an allergic reaction to PRIMAXIN occurs, discontinue the drug immediately. Serious anaphylactic reactions require immediate emergency treatment as clinically indicated.

5.2 Seizure Potential

Seizures and other CNS adverse experiences, such as confusional states and myoclonic activity, have been reported during treatment with PRIMAXIN, especially when recommended dosages were exceeded [see Adverse Reactions (6.1, 6.2)]. These experiences have occurred most commonly in patients with CNS disorders (e.g., brain lesions or history of seizures) and/or compromised renal function [see Use in Specific Populations (8.6)]. However, there have been reports of CNS adverse experiences in patients who had no recognized or documented underlying CNS disorder or compromised renal function.

Anticonvulsant therapy should be continued in patients with known seizure disorders. If focal tremors, myoclonus, or seizures occur, patients should be evaluated neurologically, placed on anticonvulsant therapy if not already instituted, and the dosage of PRIMAXIN re-examined to determine whether it should be decreased, or the antibacterial drug discontinued.

5.3 Increased Seizure Potential Due to Interaction with Valproic Acid

Case reports in the literature have shown that co-administration of carbapenems, including PRIMAXIN, to patients receiving valproic acid or divalproex sodium results in a reduction in valproic acid concentrations. The valproic acid concentrations may drop below the therapeutic range as a result of this interaction, therefore increasing the risk of breakthrough seizures. Increasing the dose of valproic acid or divalproex sodium may not be sufficient to overcome this interaction. The concomitant use of PRIMAXIN and valproic acid/divalproex sodium is generally not recommended. Antibacterials other than carbapenems should be considered to treat infections in patients whose seizures are well controlled on valproic acid or divalproex sodium. If administration of PRIMAXIN is necessary, supplemental anti-convulsant therapy should be considered [see Drug Interactions (7.3)]. Close adherence to the recommended dosage and dosage schedules is urged, especially in patients with known factors that predispose to convulsive activity.

5.4 Clostridioides difficile-Associated Diarrhea (CDAD)

Clostridioides difficile associated diarrhea (CDAD) has been reported with use of nearly all antibacterial agents, including PRIMAXIN, and may range in severity from mild diarrhea to fatal colitis. Treatment with antibacterial agents alters the normal flora of the colon leading to overgrowth of C. difficile.

C. difficile produces toxins A and B which contribute to the development of CDAD.

Hypertoxin producing strains of C. difficile cause increased morbidity and mortality, as these infections can be refractory to antimicrobial therapy and may require colectomy. CDAD must be considered in all patients who present with diarrhea following antibacterial drug use. Careful medical history is necessary since CDAD has been reported to occur over two months after the administration of antibacterial agents.

If CDAD is suspected or confirmed, ongoing antibacterial drug use not directed against C. difficile may need to be discontinued. Appropriate fluid and electrolyte management, protein supplementation, antibacterial drug treatment of C. difficile, and surgical evaluation should be instituted as clinically indicated.

5.5 Development of Drug-Resistant Bacteria

As with other antibacterial drugs, prolonged use of PRIMAXIN may result in overgrowth of nonsusceptible organisms. Repeated evaluation of the patient's condition is essential. If superinfection occurs during therapy, appropriate measures should be taken.

Prescribing PRIMAXIN in the absence of a proven or strongly suspected bacterial infection or a prophylactic indication is unlikely to provide benefit to the patient and increases the risk of the development of drug-resistant bacteria.

6 ADVERSE REACTIONS

The following serious adverse reactions are described in greater detail in the Warnings and Precautions section.

- Hypersensitivity Reactions [see Warnings and Precautions (5.1)]
- Seizure Potential [see Warnings and Precautions (5.2)]
- Increased Seizure Potential Due to Interaction with Valproic Acid [see Warnings and Precautions (5.3)]
- Clostridioides difficile-Associated Diarrhea (CDAD) [see Warnings and Precautions (5.4)]
- Development of Drug-Resistant Bacteria [see Warnings and Precautions (5.5)]

6.1 Clinical Trials Experience

Because clinical trials are conducted under widely varying conditions, adverse reaction rates observed in the clinical trials of a drug cannot be directly compared to rates in the clinical trials of another drug and may not reflect the rates observed in practice.

Adult Patients

During clinical investigations 1,723 patients were treated with PRIMAXIN. Table 4 shows the incidence of adverse reactions reported during the clinical investigations of adult patients treated with PRIMAXIN.

Table 4: Incidence (%) [Adverse reactions with an incidence ≥0.2% of PRIMAXIN-treated adult patients.] of Adverse Reactions Reported During Clinical Investigations of Adult Patients Treated with PRIMAXIN
Body System | Adverse Reactions | Frequency (%)
Local Administration site | Phlebitis/thrombophlebitis | 3.1%
 | Pain at the injection site | 0.7%
 | Erythema at the injection site | 0.4%
 | Vein induration | 0.2%
Gastrointestinal | Nausea | 2.0%
 | Diarrhea | 1.8%
 | Vomiting | 1.5%
Skin | Rash | 0.9%
 | Pruritus | 0.3%
 | Urticaria | 0.2%
Vascular | Hypotension | 0.4%
Body as a Whole | Fever | 0.5%
Nervous system | Seizures | 0.4%
 | Dizziness | 0.3%
 | Somnolence | 0.2%

Additional adverse reactions reported in less than 0.2% of the patients or reported since the drug was marketed are listed within each body system in order of decreasing severity [see Table 5].

Table 5: Additional Adverse Reactions Occurring in Less than 0.2% of Adult Patients Listed within Each Body System in Order of Decreasing Severity
Body System | Adverse Reactions
Gastrointestinal | Pseudomembranous Colitis (the onset of Pseudomembranous colitis symptoms), Hemorrhagic Colitis
 | Pseudomembranous Colitis (the onset of Pseudomembranous colitis symptoms), Hemorrhagic Colitis
 | Gastroenteritis
 | Abdominal Pain
 | Glossitis
 | Tongue Papillar
 | Hypertrophy
 | Heartburn
 | Pharyngeal Pain
 | Increased Salivation
CNS | Encephalopathy
 | Confusion
 | Myoclonus
 | Paresthesia
 | Vertigo
 | Headache
Special Senses | Hearing Loss
 | Tinnitus
Respiratory | Chest Discomfort
 | Dyspnea
 | Hyperventilation
 | Thoracic Spine Pain
Cardiovascular | Palpitations
 | Tachycardia
Skin | Erythema Multiforme
 | Angioneurotic Edema
 | Flushing
 | Cyanosis
 | Hyperhidrosis
 | Skin Texture Changes
 | Candidiasis
 | Pruritus Vulvae
Local Administration site | Infused vein infection
Body as a Whole | Polyarthralgia
 | Asthenia/Weakness
Renal | Oliguria/Anuria
 | Polyuria

Adverse Laboratory Changes

The following adverse laboratory changes were reported during clinical trials:

Hepatic: Increased alanine aminotransferase (ALT or SGPT), aspartate aminotransferase (AST or SGOT), alkaline phosphatase, bilirubin, and lactate dehydrogenase (LDH)

Hemic: Increased eosinophils, positive Coombs test, increased WBC, increased platelets, decreased hemoglobin and hematocrit, increased monocytes, abnormal prothrombin time, increased lymphocytes, increased basophils

Electrolytes: Decreased serum sodium, increased potassium, increased chloride

Renal: Increased BUN, creatinine

Urinalysis: Presence of urine protein, urine red blood cells, urine white blood cells, urine casts, urine bilirubin, and urine urobilinogen.

Pediatric Patients

Table 6: Incidence (%) [Adverse reactions that occurred in >1% of PRIMAXIN-treated pediatric patients (greater than or equal to 3 months of age)] of Adverse Reactions Reported During Clinical Investigations of Pediatric Patients Greater Than or Equal to 3 Months of Age Treated with PRIMAXIN
Body System | Adverse Reactions | Frequency (%)
Local Administration Site | Phlebitis | 2.2%
 | Intravenous Site Irritation | 1.1%
Gastrointestinal | Diarrhea | 3.9%
 | Gastroenteritis | 1.1%
 | Vomiting | 1.1%
Skin | Rash | 2.2%
Renal | Urine Discoloration | 1.1%

Table 7: Incidence (%) [Adverse reactions that occurred in >1% of PRIMAXIN-treated pediatric patients (neonates to 3 months of age)] of Adverse Reactions Reported During Clinical Investigations of Pediatric Patients Neonates to 3 Months of Age Treated with PRIMAXIN
Body System | Adverse Reactions | Frequency (%)
Gastrointestinal | Diarrhea | 3%
CNS | Convulsions | 5.9%
Cardiovascular | Tachycardia | 1.5%
Skin | Rash | 1.5%
Body as a Whole | Oral Candidiasis | 1.5%
Renal | Oliguria/Anuria | 2.2%

Adverse Laboratory Changes

The following adverse laboratory changes were reported in studies of 178 pediatric patients 3 months of age: increased AST (SGOT), decreased hemoglobin/hematocrit, increased platelets, increased eosinophils, increased ALT (SGPT), increased urine protein, decreased neutrophils.

The following adverse laboratory changes were reported in studies of 135 patients (neonates to 3 months of age): increased eosinophils, increased AST (SGPT), increased serum creatinine, increased/decreased platelet count, increased/decreased bilirubin, increased ALT (SGPT), increased alkaline phosphatase, increased/decreased hematocrit.

6.2 Postmarketing Experience

The following adverse reactions have been identified during post-approval use of PRIMAXIN. Because these reactions are reported voluntarily from a population of uncertain size, it is not always possible to reliably estimate their frequency or establish a causal relationship to drug exposure.

Table 8: Adverse Reactions Identified During Post Approval Use of PRIMAXIN
Body System | Adverse Reactions
Gastrointestinal | Hepatitis (including fulminant hepatitis)
 | Hepatic failure
 | Jaundice
 | Staining of the teeth and/or tongue
Hematologic | Pancytopenia
 | Bone marrow depression
 | Thrombocytopenia
 | Neutropenia
 | Leukopenia
 | Hemolytic anemia
CNS | Tremor
 | Psychic disturbances including hallucinations
 | Dyskinesia
 | Agitation
Special Senses | Taste perversion
Skin | Stevens-Johnson syndrome
 | Toxic epidermal necrolysis
Body as a whole | Drug fever
Renal | Acute renal failure
 | Urine discoloration

Adverse Laboratory Changes

Adverse laboratory changes reported since the drug was marketed were:

Hematologic: agranulocytosis.

Examination of published literature and spontaneous adverse reactions reports suggested a similar spectrum of adverse reactions in adult and pediatric patients.

7 DRUG INTERACTIONS

7.1 Ganciclovir

Generalized seizures have been reported in patients who received ganciclovir and PRIMAXIN. These drugs should not be used concomitantly with PRIMAXIN unless the potential benefits outweigh the risks.

7.2 Probenecid

Concomitant administration of PRIMAXIN and probenecid results in increases in the plasma level and half-life of imipenem. Therefore, it is not recommended that probenecid be given concomitantly with PRIMAXIN.

7.3 Valproic Acid

Case reports in the literature have shown that co-administration of carbapenems, including PRIMAXIN, to patients receiving valproic acid or divalproex sodium results in a reduction in valproic acid concentrations. The valproic acid concentrations may drop below the therapeutic range as a result of this interaction, therefore increasing the risk of breakthrough seizures. Although the mechanism of this interaction is unknown, data from in vitro and animal studies suggest that carbapenems may inhibit the hydrolysis of valproic acid's glucuronide metabolite (VPA-g) back to valproic acid, thus decreasing the serum concentrations of valproic acid [see Warnings and Precautions (5.3)]. The concomitant use of PRIMAXIN and valproic acid/divalproex sodium is generally not recommended. Antibacterials other than carbapenems should be considered to treat infections in patients whose seizures are well-controlled on valproic acid or divalproex sodium.

8 USE IN SPECIFIC POPULATIONS

8.1 Pregnancy

Risk Summary

Available data from a small number of postmarketing cases with PRIMAXIN use in pregnancy are not sufficient to identify any drug-associated risks for major birth defects, miscarriage, or adverse maternal or fetal outcomes.

Developmental toxicity studies with imipenem and cilastatin sodium (alone or in combination) administered to mice, rats, rabbits, and monkeys at doses 0.4 to 2.9 times the recommended human dose (RHD), (based on body surface area), showed no drug-induced fetal malformations.

Embryofetal development studies with imipenem/cilastatin administered to cynomolgus monkeys at doses similar to the RHD (based on body surface area) showed an increase in embryonic loss (see Data).

The background risk of major birth defects and miscarriage for the indicated populations is unknown. All pregnancies have a background risk of birth defect, loss, or other adverse outcomes. The background risk of major birth defects is 2-4% and of miscarriage is 15-20% of clinically recognized pregnancies within the general population.

Data

Animal Data

Reproductive toxicity studies with imipenem and cilastatin (alone or in combination) administered to mice, rats, and rabbits showed no evidence of effects on embryofetal (mice, rats and rabbits) or pre/postnatal (rats) development.

Imipenem was administered intravenously to rats (gestation days (GD) 7 to 17) and rabbits (GD 6 to 18) at doses up to 900 and 60 mg/kg/day, respectively, approximately 2.9 and 0.4 times the RHD (based on body surface area).

Cilastatin was administered subcutaneously to rats (GD 6 to 17) and intravenously to rabbits (GD 6 to 18) at doses up to 1000 and 300 mg/kg/day, respectively, approximately 3.2 and 1.9 times the RHD (based on body surface area).

Imipenem/cilastatin was administered intravenously to mice at doses up to 320 mg/kg/day (GD 6 to 15). In two separate studies, imipenem/cilastatin was administered to rats (GD 6 to 17 and GD 15 to day 21 postpartum) both intravenously at doses up to 80 mg/kg/day and subcutaneously at 320 mg/kg/day. The higher dose is approximately equal to the RHD (based on body surface area).

Imipenem/cilastatin administered intravenously to pregnant cynomolgus monkeys during organogenesis at 100 mg/kg/day, approximately 0.6 times the RHD (based on body surface area), at an infusion rate mimicking human clinical use, was not associated with fetal malformations, but there was an increase in embryonic loss relative to controls. Imipenem/cilastatin administered to pregnant cynomolgus monkeys during organogenesis at 40 mg/kg/day by bolus intravenous injection caused significant maternal toxicity including death and embryofetal loss.

8.2 Lactation

Risk Summary

There are insufficient data on the presence of imipenem/cilastatin in human milk, and no data on the effects on the breastfed child, or the effects on milk production. The developmental and health benefits of breastfeeding should be considered along with the mother's clinical need for PRIMAXIN and any potential adverse effects on the breastfed child from PRIMAXIN or from the underlying maternal condition.

8.4 Pediatric Use

Use of PRIMAXIN in pediatric patients is supported by evidence from adequate and well-controlled trials of PRIMAXIN in adults and clinical studies in pediatric patients [see Dosage and Administration (2.2) and Clinical Pharmacology (12.3)].

PRIMAXIN is not recommended in pediatric patients with CNS infections because of the risk of seizures.

PRIMAXIN is not recommended in pediatric patients less than 30 kg with renal impairment, as no data are available.

8.5 Geriatric Use

Of the approximately 3600 subjects ≥18 years of age in clinical studies of PRIMAXIN, including postmarketing studies, approximately 2800 received PRIMAXIN. Of the subjects who received PRIMAXIN, data are available on approximately 800 subjects who were 65 and over, including approximately 300 subjects who were 75 and over. No overall differences in safety or effectiveness were observed between these subjects and younger subjects. Other reported clinical experience has not identified differences in responses between the elderly and younger patients, but greater sensitivity of some older individuals cannot be ruled out.

This drug is known to be substantially excreted by the kidney, and the risk of toxic reactions to this drug may be greater in patients with impaired renal function. Because elderly patients are more likely to have decreased renal function, care should be taken in dose selection, and it may be useful to monitor renal function.

No dosage adjustment is required based on age [see Clinical Pharmacology (12.3)]. Dosage adjustment in the case of renal impairment is necessary [see Dosage and Administration (2.3)].

8.6 Renal Impairment

Dosage adjustment is necessary in patients with renal impairment [see Dosage and Administration (2.3)]. Adult patients with creatinine clearances of less than or equal to 30 mL/min, whether or not undergoing hemodialysis, had a higher risk of seizure activity than those without impairment of renal function [see Warnings and Precautions (5.2)]. Therefore, close adherence to the dosing guidelines and regular monitoring of creatinine clearance for these patients is recommended.

10 OVERDOSAGE

In the case of overdosage, discontinue PRIMAXIN, treat symptomatically, and institute supportive measures as required. PRIMAXIN is hemodialyzable.

11 DESCRIPTION

PRIMAXIN (imipenem and cilastatin) for Injection is a sterile formulation of imipenem, a penem antibacterial, and cilastatin, a renal dehydropeptidase inhibitor with sodium bicarbonate added as a buffer. PRIMAXIN is an antibacterial drug for intravenous administration.

Imipenem (N-formimidoylthienamycin monohydrate) is a crystalline derivative of thienamycin, which is produced by Streptomyces cattleya. Its chemical name is (5R,6S)-3-[[2-(formimidoylamino)ethyl]thio]-6-[(R)-1-hydroxyethyl]-7-oxo-1-azabicyclo[3.2.0]hept-2-ene-2-carboxylic acid monohydrate. It is an off-white, nonhygroscopic crystalline compound with a molecular weight of 317.37. It is sparingly soluble in water and slightly soluble in methanol. Its empirical formula is C12H17N3O4S∙H2O, and its structural formula is:

Cilastatin sodium is the sodium salt of a derivatized heptenoic acid. Its chemical name is sodium (Z)-7[[(R)-2-amino-2-carboxyethyl]thio]-2-[(S)-2,2-dimethylcyclopropanecarboxamido]-2-heptenoate. It is an off-white to yellowish-white, hygroscopic, amorphous compound with a molecular weight of 380.43. It is very soluble in water and in methanol. Its empirical formula is C16H25N2O5SNa, and its structural formula is:

Each single-dose vial of PRIMAXIN contains 500 mg imipenem (equivalent to 530 mg imipenem monohydrate), 500 mg cilastatin (equivalent to 531 mg cilastatin sodium), and 20 mg sodium bicarbonate (used as a buffer). PRIMAXIN is buffered to provide solutions in the pH range of 6.5 to 8.5. There is no significant change in pH when solutions are prepared and used as directed [see How Supplied/Storage and Handling (16.1)]. PRIMAXIN 500 contains 37.5 mg of sodium (1.6 mEq). Solutions of PRIMAXIN range from colorless to yellow. Variations of color within this range do not affect the potency of the product.

12 CLINICAL PHARMACOLOGY

12.1 Mechanism of Action

PRIMAXIN is a combination of imipenem and cilastatin. Imipenem is a penem antibacterial drug [see Microbiology (12.4)]. Cilastatin is a renal dehydropeptidase inhibitor that limits the renal metabolism of imipenem.

12.3 Pharmacokinetics

Intravenous infusion of PRIMAXIN over 20 minutes results in peak plasma levels of imipenem antimicrobial activity that range from 21 to 58 mcg/mL for the 500 mg dose, and from 41 to 83 mcg/mL for the 1000 mg dose. At these doses, plasma levels of imipenem antimicrobial activity decline to below 1 mcg/mL or less in 4 to 6 hours. Peak plasma levels of cilastatin following a 20-minute intravenous infusion of PRIMAXIN range from 31 to 49 mcg/mL for the 500 mg dose, and from 56 to 88 mcg/mL for the 1000 mg dose.

Distribution

The binding of imipenem to human serum proteins is approximately 20% and that of cilastatin is approximately 40%.

Imipenem has been shown to penetrate into human tissues, including vitreous humor, aqueous humor, lung, peritoneal fluid, CSF, bone, interstitial fluid, skin, and fascia. As there are no adequate and well-controlled studies of imipenem treatment in these additional body sites, the clinical significance of these tissue concentration data is unknown.

After a 1 gram dose of PRIMAXIN, the following average levels of imipenem were measured (usually at 1 hour post dose except where indicated) in the tissues and fluids listed in Table 9:

Table 9: Average Levels of Imipenem
Tissue or Fluid | N | Imipenem Level mcg/mL or mcg/g | Range
Vitreous Humor | 3 | 3.4 (3.5 hours post dose) | 2.88–3.6
Aqueous Humor | 5 | 2.99 (2 hours post dose) | 2.4–3.9
Lung Tissue | 8 | 5.6 (median) | 3.5–15.5
Sputum | 1 | 2.1 | —
Pleural | 1 | 22.0 | —
Peritoneal | 12 | 23.9 S.D.±5.3 (2 hours post dose) | —
Bile | 2 | 5.3 (2.25 hours post dose) | 4.6–6.0
CSF (uninflamed) | 5 | 1.0 (4 hours post dose) | 0.26–2.0
CSF (inflamed) | 7 | 2.6 (2 hours post dose) | 0.5–5.5
Fallopian Tubes | 1 | 13.6 | —
Endometrium | 1 | 11.1 | —
Myometrium | 1 | 5.0 | —
Bone | 10 | 2.6 | 0.4–5.4
Interstitial Fluid | 12 | 16.4 | 10.0–22.6
Skin | 12 | 4.4 | NA
Fascia | 12 | 4.4 | NA

Metabolism

Imipenem, when administered alone, is metabolized in the kidneys by dehydropeptidase I, resulting in relatively low levels in urine. Cilastatin, an inhibitor of this enzyme, effectively prevents renal metabolism of imipenem so that when imipenem and cilastatin sodium are given concomitantly, adequate antibacterial levels of imipenem are achieved in the urine.

Elimination

The plasma half-life of each component is approximately 1 hour. Approximately 70% of the administered imipenem is recovered in the urine within 10 hours after which no further urinary excretion is detectable. Urine concentrations of imipenem in excess of 10 mcg/mL can be maintained for up to 8 hours with PRIMAXIN at the 500 mg dose. Approximately 70% of the cilastatin sodium dose is recovered in the urine within 10 hours of administration of PRIMAXIN. PRIMAXIN is hemodialyzable [see Overdosage (10)].

No accumulation of imipenem/cilastatin in plasma or urine is observed with regimens administered as frequently as every 6 hours in patients with normal renal function.

Specific Populations

Geriatric Patients

In healthy elderly volunteers (65 to 75 years of age with normal renal function for their age), the pharmacokinetics of a single dose of imipenem 500 mg and cilastatin 500 mg administered intravenously over 20 minutes are consistent with those expected in subjects with slight renal impairment for which no dosage alteration is considered necessary. The mean plasma half-lives of imipenem and cilastatin are 91±7 minutes and 69±15 minutes, respectively. Multiple dosing has no effect on the pharmacokinetics of either imipenem or cilastatin, and no accumulation of imipenem/cilastatin is observed.

Pediatric Patients

Doses of 25 mg/kg/dose in patients 3 months to <3 years of age, and 15 mg/kg/dose in patients 3-12 years of age were associated with mean trough plasma concentrations of imipenem of 1.1±0.4 mcg/mL and 0.6±0.2 mcg/mL following multiple 60-minute infusions, respectively; trough urinary concentrations of imipenem were in excess of 10 mcg/mL for both doses. These doses have provided adequate plasma and urine concentrations for the treatment of non-CNS infections.

In a dose-ranging study of smaller premature infants (670-1,890 g) in the first week of life, a dose of 20 mg/kg q12h by 15-30 minutes infusion was associated with mean peak and trough plasma imipenem concentrations of 43 mcg/mL and 1.7 mcg/mL after multiple doses, respectively. However, moderate accumulation of cilastatin in neonates may occur following multiple doses of PRIMAXIN. The safety of this accumulation is unknown.

12.4 Microbiology

Mechanism of Action

PRIMAXIN is a combination of imipenem and cilastatin. The bactericidal activity of imipenem results from the inhibition of cell wall synthesis. Its greatest affinity is for penicillin binding proteins (PBPs) 1A, 1B, 2, 4, 5 and 6 of Escherichia coli, and 1A, 1B, 2, 4 and 5 of Pseudomonas aeruginosa. The lethal effect is related to binding to PBP 2 and PBP 1B.

Imipenem has a high degree of stability in the presence of beta-lactamases, both penicillinases and cephalosporinases produced by Gram-negative and Gram-positive bacteria. It is a potent inhibitor of beta-lactamases from certain Gram-negative bacteria which are inherently resistant to most beta-lactam antibacterials, e.g., Pseudomonas aeruginosa, Serratia spp., and Enterobacter spp.

Resistance

Imipenem is inactive in vitro against Enterococcus faecium, Stenotrophomonas maltophilia and some isolates of Burkholderia cepacia. Methicillin-resistant staphylococci should be reported as resistant to imipenem.

Interaction with Other Antimicrobials

In vitro tests show imipenem to act synergistically with aminoglycoside antibacterials against some isolates of Pseudomonas aeruginosa.

Antimicrobial Activity

Imipenem has been shown to be active against most isolates of the following microorganisms, both in vitro and in clinical infections [see Indications and Usage (1)].

Aerobic bacteria

Gram-positive bacteria
Enterococcus faecalis
Staphylococcus aureus
Staphylococcus epidermidis
Streptococcus agalactiae (Group B streptococci)
Streptococcus pneumoniae
Streptococcus pyogenes

Gram-negative bacteria
Acinetobacter spp.
Citrobacter spp.
Enterobacter spp.
Escherichia coli
Gardnerella vaginalis
Haemophilus influenzae
Haemophilus parainfluenzae
Klebsiella spp.
Morganella morganii
Proteus vulgaris
Providencia rettgeri
Pseudomonas aeruginosa
Serratia spp., including S. marcescens

Anaerobic bacteria

Gram-positive bacteria
Bifidobacterium spp.
Clostridium spp.
Eubacterium spp.
Peptococcus spp.
Peptostreptococcus spp.
Propionibacterium spp.

Gram-negative bacteria
Bacteroides spp., including B. fragilis
Fusobacterium spp.

The following in vitro data are available, but their clinical significance is unknown. At least 90 percent of the following bacteria exhibit an in vitro minimum inhibitory concentration (MIC) less than or equal to the susceptible breakpoint for imipenem against isolates of similar genus or organism group. However, the efficacy of imipenem in treating clinical infections due to these bacteria has not been established in adequate and well-controlled clinical trials.

Aerobic bacteria

Gram-positive bacteria
Bacillus spp.
Listeria monocytogenes
Nocardia spp.
Staphylococcus saprophyticus
Group C streptococci
Group G streptococci
Viridans group streptococci

Gram-negative bacteria
Aeromonas hydrophila
Alcaligenes spp.
Capnocytophaga spp.
Haemophilus ducreyi
Neisseria gonorrhoeae
Pasteurella spp.
Providencia stuartii

Anaerobic bacteria

Prevotella bivia
Prevotella disiens
Prevotella melaninogenica
Veillonella spp.

Susceptibility Testing

For specific information regarding susceptibility test methods, interpretive criteria, and associated test methods and quality control standards recognized by FDA for this drug, please see: https://www.fda.gov/STIC.

13 NONCLINICAL TOXICOLOGY

13.1 Carcinogenesis, Mutagenesis, Impairment of Fertility

Long term studies in animals have not been performed to evaluate carcinogenic potential of imipenem/cilastatin. A variety of bacterial and mammalian tests were performed to evaluate genetic toxicity. The tests used were: V79 mammalian cell mutagenesis assay (cilastatin sodium alone and imipenem alone), Ames test (cilastatin sodium alone and imipenem alone), unscheduled DNA synthesis assay (imipenem/cilastatin sodium) and in vivo mouse cytogenetics test (imipenem/cilastatin sodium). None of these tests showed any evidence of genetic alterations.

Impairment of fertility or reproductive performance was not observed in male and female rats given imipenem/cilastatin at intravenous doses up to 80 mg/kg/day and at a subcutaneous dose of 320 mg/kg/day. In rats, a dose of 320 mg/kg/day was approximately equal to the highest recommended human dose based on body surface area.

16 HOW SUPPLIED/STORAGE AND HANDLING

16.1 How Supplied

PRIMAXIN is supplied as a sterile powder mixture in single dose containers including vials containing imipenem (anhydrous equivalent) and cilastatin (free acid equivalent) as follows:

Each PRIMAXIN Package Contains: | National Drug Code (NDC) Number
A tray of 25 vials, each vial containing 500 mg imipenem equivalent, 500 mg cilastatin equivalent, and 20 mg sodium bicarbonate as a buffer. | (NDC 0006-3516-59)

16.2 Storage and Handling

Before Reconstitution:

PRIMAXIN dry powder should be stored at a temperature below 25°C (77°F).

17 PATIENT COUNSELING INFORMATION

- Advise patients that allergic reactions, including serious allergic reactions, could occur and that serious reactions require immediate treatment. They should report any previous hypersensitivity reactions to PRIMAXIN, other carbapenems, beta-lactams or other allergens.
- Counsel patients that antibacterial drugs including PRIMAXIN should only be used to treat bacterial infections. They do not treat viral infections (e.g., the common cold). When PRIMAXIN is prescribed to treat a bacterial infection, patients should be told that although it is common to feel better early in the course of therapy, the medication should be taken exactly as directed. Skipping doses or not completing the full course of therapy may (1) decrease the effectiveness of the immediate treatment and (2) increase the likelihood that bacteria will develop resistance and will not be treatable by PRIMAXIN or other antibacterial drugs in the future.
- Counsel patients to inform their physician:
  - if they have central nervous system disorders such as stroke or history of seizures. Seizures have been reported during treatment with PRIMAXIN and with closely related antibacterial drugs.
  - if they are taking valproic acid or sodium valproate. Valproic acid concentrations in the blood may drop below the therapeutic range upon co-administration with PRIMAXIN. If treatment with PRIMAXIN is necessary and continued, alternative or supplemental anti-convulsant medication to prevent and/or treat seizures may be needed.
- Advise patients that diarrhea is a common problem caused by antibacterial drugs and usually resolves when the drug is discontinued. Sometimes, frequent watery or bloody diarrhea may occur and may be a sign of a more serious intestinal infection. If severe watery or bloody diarrhea develops, patients should contact their healthcare provider.

Merck Sharp & Dohme LLC
Rahway, NJ 07065, USA

Copyright © 1985-2022 Merck & Co., Inc., Rahway, NJ, USA, and its affiliates.
All rights reserved.

uspi-mk0787b-iv-2205r045

PRINCIPAL DISPLAY PANEL 250 mg Vial Label

NDC 0006-3514-58

250
PRIMAXIN® I.V.
(IMIPENEM AND CILASTATIN FOR INJECTION)

IMIPENEM 250 mg (Anhydrous Equivalent)
CILASTATIN EQUIVALENT 250 mg
CAUTION: SINGLE DOSE VIAL / FOR I.V. USE ONLY
NOT FOR DIRECT INFUSION

Rx only
250 mg

Merck Sharp & Dohme Corp., a subsidiary of
MERCK & CO., INC., Whitehouse Station, NJ 08889, USA

3514

PRINCIPAL DISPLAY PANEL 500 mg Vial Label

NDC 0006-3516-59

500
PRIMAXIN® I.V.
(IMIPENEM AND CILASTATIN FOR INJECTION)

Each vial contains 500 mg imipenem (equivalent to 530 mg
imipenem monohydrate), 500 mg cilastatin (equivalent to 531 mg
cilastatin sodium), and 20 mg sodium bicarbonate (used as a buffer).

CAUTION: SINGLE DOSE VIAL / FOR I.V. USE ONLY
NOT FOR DIRECT INFUSION

Rx only
500 mg

PRINCIPAL DISPLAY PANEL - 500 mg Vial Package

1 PACKAGE (25 VIALS)
NDC 0006-3516-59

500
PRIMAXIN® I.V.
(IMIPENEM AND CILASTATIN FOR INJECTION)

Not to be divided.

Each vial contains 500 mg imipenem (equivalent to 530 mg imipenem monohydrate), 500 mg cilastatin
(equivalent to 531 mg cilastatin sodium), and 20 mg sodium bicarbonate (used as a buffer).
CAUTION: SINGLE DOSE VIAL / FOR I.V. USE ONLY / NOT FOR DIRECT INFUSION
For the Preparation of Intravenous Solutions and USUAL ADULT DOSAGE: See
accompanying circular. Color changes in solution from colorless to
yellow do not affect potency. Store dry material below 25ºC.

Rx only

Merck Sharp & Dohme LLC
Rahway, NJ 07065, USA

Copyright © 2022 Merck & Co., Inc.
Rahway, NJ, USA, and its affiliates.
All rights reserved.

PRINCIPAL DISPLAY PANEL - Single-Dose ADD-Vantage Vial 250 mg

NDC 0006-3551-58

Single-dose ADD-Vantage® vial

250

PRIMAXIN® I.V.

(IMIPENEM AND CILASTATIN FOR INJECTION)

IMIPENEM 250 mg (Anhydrous Equivalent)
CILASTATIN EQUIVALENT 250 mg

CAUTION: SINGLE DOSE VIAL / FOR I.V. USE ONLY
NOT FOR DIRECT INFUSION

PRIMAXIN is a registered trademark of Merck Sharp & Dohme Corp.

ADD-Vantage is a registered trademark of ABBOTT LABORATORIES, Inc.

9960800

For the Preparation of Intravenous Solutions and USUAL ADULT DOSAGE: See accompanying circular.

Store dry material below 25°C.

After constitution as directed, the solution maintains satisfactory potency for 4 hours at room temperature.

Consult accompanying INSTRUCTIONS FOR USE.

Use only with ADD-Vantage® Diluent Containers.

Rx only

250 mg | No. 3551

Merck Sharp & Dohme Corp., a subsidiary of
MERCK & CO., INC.
Whitehouse Station, NJ 08889, USA

PRINCIPAL DISPLAY PANEL - Single-Dose ADD-Vantage Vial 500 mg

NDC 0006-3552-59

Single-dose ADD-Vantage® vial

500

PRIMAXIN® I.V.

(IMIPENEM AND CILASTATIN FOR INJECTION)

IMIPENEM 500 mg (Anhydrous Equivalent)
CILASTATIN EQUIVALENT 500 mg

CAUTION: SINGLE DOSE VIAL / FOR I.V. USE ONLY
NOT FOR DIRECT INFUSION

PRIMAXIN is a registered trademark of Merck Sharp & Dohme Corp.

ADD-Vantage is a registered trademark of ABBOTT LABORATORIES, Inc.

9940700

For the Preparation of Intravenous Solutions and USUAL ADULT DOSAGE: See accompanying circular.

Store dry material below 25°C.

After constitution as directed, the solution maintains satisfactory potency for 4 hours at room temperature.

Consult accompanying INSTRUCTIONS FOR USE.

Use only with ADD-Vantage® Diluent Containers.

Rx only

500 mg | No. 3552

Merck Sharp & Dohme Corp., a subsidiary of
MERCK & CO., INC.
Whitehouse Station, NJ 08889, USA